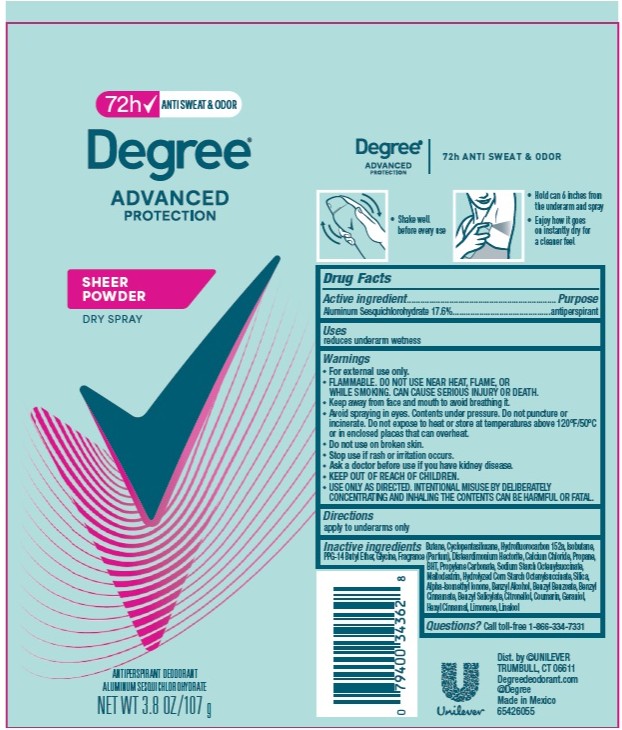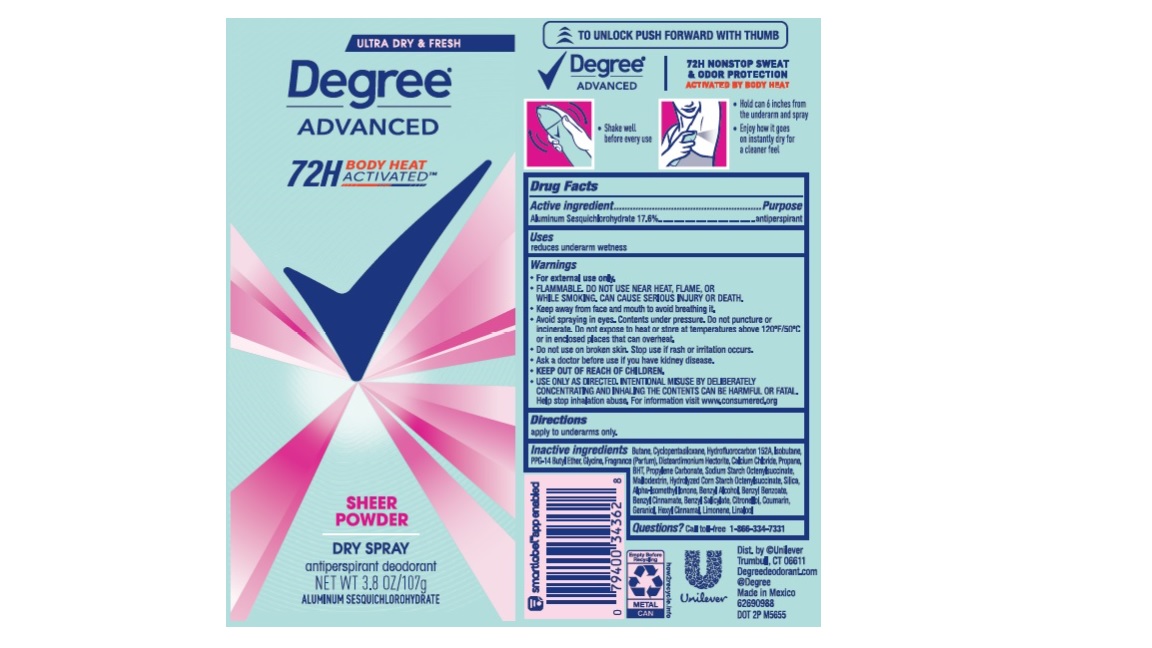 DRUG LABEL: Degree
NDC: 64942-2180 | Form: AEROSOL, SPRAY
Manufacturer: Conopco, Inc. d/b/a Unilever
Category: otc | Type: HUMAN OTC DRUG LABEL
Date: 20260210

ACTIVE INGREDIENTS: ALUMINUM SESQUICHLOROHYDRATE 17.6 g/100 g
INACTIVE INGREDIENTS: 1,1-DIFLUOROETHANE; CYCLOMETHICONE 5; PPG-14 BUTYL ETHER; DISTEARDIMONIUM HECTORITE; CALCIUM CHLORIDE; GERANIOL; ISOMETHYL-.ALPHA.-IONONE; BENZYL ALCOHOL; BENZYL CINNAMATE; .ALPHA.-HEXYLCINNAMALDEHYDE; LINALOOL, (+/-)-; PROPANE; BUTYLATED HYDROXYTOLUENE; PROPYLENE CARBONATE; MALTODEXTRIN; SILICON DIOXIDE; GLYCINE; BENZYL SALICYLATE; COUMARIN; LIMONENE, (+)-; BENZYL BENZOATE; ISOBUTANE; .BETA.-CITRONELLOL, (R)-; BUTANE

Degree Advanced Sheer Powder Dry Spray 72H Antiperspirant Deodorant

Drug Facts

Active ingredient

Aluminum Sesquichlorohydrate (17.6%)

Purpose

antiperspirant

Uses

reduces underarm wetness

Directions

For underarms use only

Inactive ingredients

Butane, Cyclopentasiloxane, Hydrofluorocarbon 152a, Isobutane, PPG-14 Butyl Ether, Glycine, Fragrance (Parfum), Disteardimonium Hectorite, Calcium Chloride, Propane, BHT, Propylene Carbonate, Sodium Starch Octenylsuccinate, Maltodextrin, Hydrolyzed Corn Starch Octenylsuccinate, Silica, Alpha-Isomethyl Ionone, Benzyl Alcohol, Benzyl Benzoate, Benzyl Cinnamate, Benzyl Salicylate, Citronellol, Coumarin, Geraniol, Hexyl Cinnamal, Limonene, Linalool

Questions?

Call toll-free 1-866-334-7331